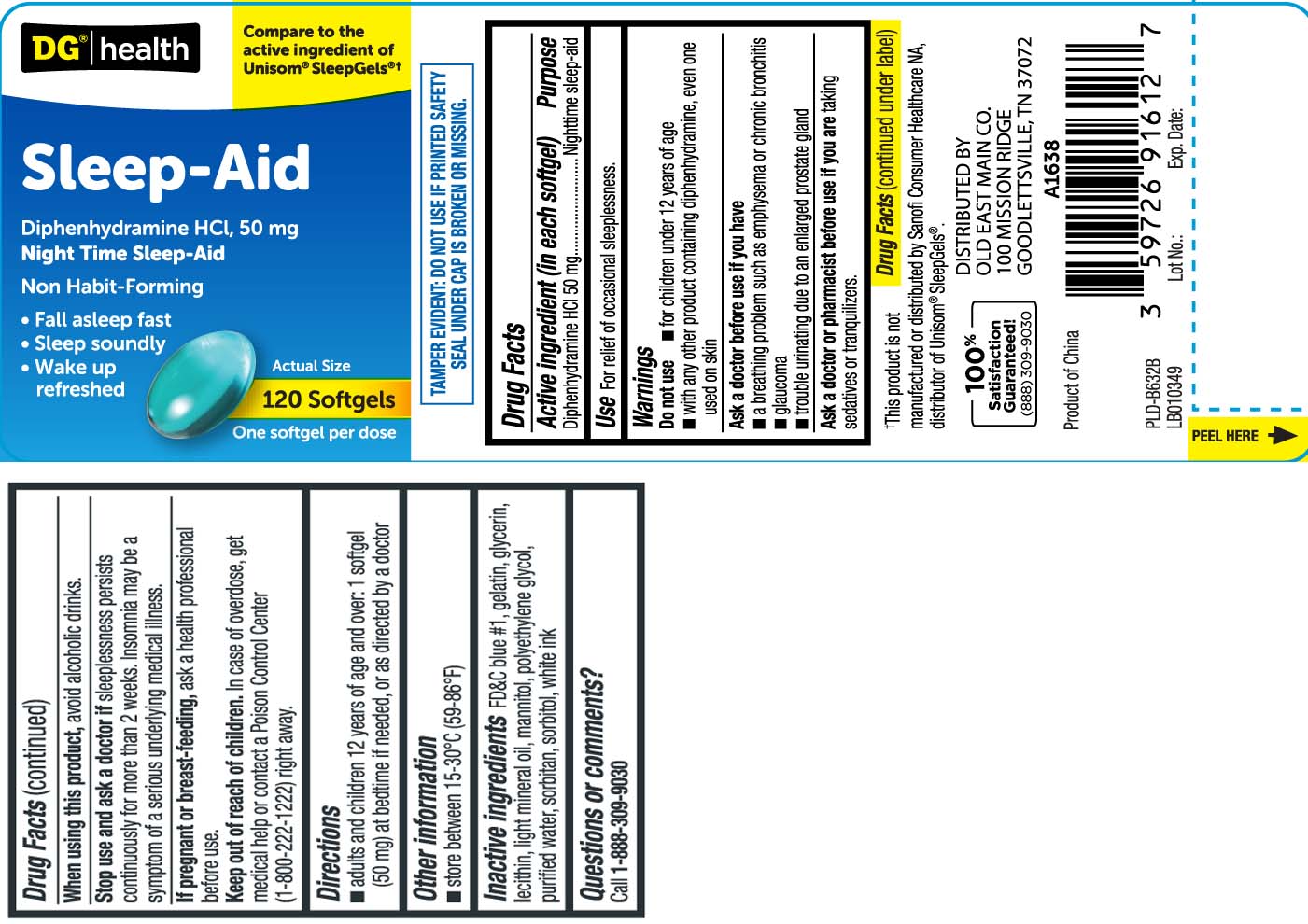 DRUG LABEL: Sleep Aid
NDC: 55910-916 | Form: CAPSULE
Manufacturer: Dolgencorp, Inc.  (DOLLAR GENERAL & REXALL)
Category: otc | Type: HUMAN OTC DRUG LABEL
Date: 20260128

ACTIVE INGREDIENTS: DIPHENHYDRAMINE HYDROCHLORIDE 50 mg/1 1
INACTIVE INGREDIENTS: FD&C BLUE NO. 1; GELATIN; GLYCERIN; POLYETHYLENE GLYCOL, UNSPECIFIED; LECITHIN, SOYBEAN; WATER; SORBITOL; SORBITAN; LIGHT MINERAL OIL; MANNITOL

Drug Facts

Active ingredient (in each softgel)

Diphenhydramine HCl 50 mg

Purpose

Nighttime sleep-aid

Uses

For relief of occasional sleeplessness.

Warnings

Do not use

- for children under 12 years of age
- with any other product containing diphenhydramine, even one used on skin

Ask a doctor before use if you have

- a breathing problem such as emphysema or chronic bronchitis
- glaucoma
- trouble urinating due to an enlarged prostate gland

Ask a doctor or pharmacist before use if you are

taking sedatives or tranquilizers.

When using this product

avoid alcoholic drinks

Stop use and ask a doctor if

sleeplessness persists continuously for more than 2 weeks. Insomnia may be a symptom of a serious underlying medical illness.

If pregnant or breast-feeding,

ask a health professional before use.

Keep out of reach of children.

In case of overdose, get medical help or contact a Poison Control Center (1-800-222-1222) right away.

Directions

- adults and children 12 years of age and over: 1 softgel (50 mg) at bedtime if needed, or as directed by a doctor

Other information

- store between 15-30ºC (59-86ºF)

Inactive ingredients

FD&C blue #1, gelatin, glycerin, lecithin, light mineral oil, mannitol, polyethylene glycol, purified water, sorbitan, sorbitol, white ink

Questions or comments?

Call 1-888-309-9030

Principal Display Panel

Compare to the active ingredient of Unisom® SleepGels®†

Sleep-Aid

Diphenhydramine HCl, 50 mg

Night Time Sleep-Aid

Non Habit-Forming

- Fall asleep fast
- Sleep soundly
- Wake up refreshed

Softgels

One softgel per dose

†This product is not manufactured or distributed by Sanofi Consumer Healthcare NA, distributor of Unisom® SleepGels®.

TAMPER EVIDENT: DO NOT USE IF PRINTED SAFETY SEAL UNDER CAP IS BROKEN OR MISSING.

KEEP OUTER CARTON FOR COMPLETE WARNINGS AND PRODUCT INFORMATION.

DISTRIBUTED BY OLD EAST MAIN CO.

100 MISSION RIDGE

GOODLETTSVILLE, TN 37072

Product Label

DOLLAR GENERAL HEALTH Sleep-Aid